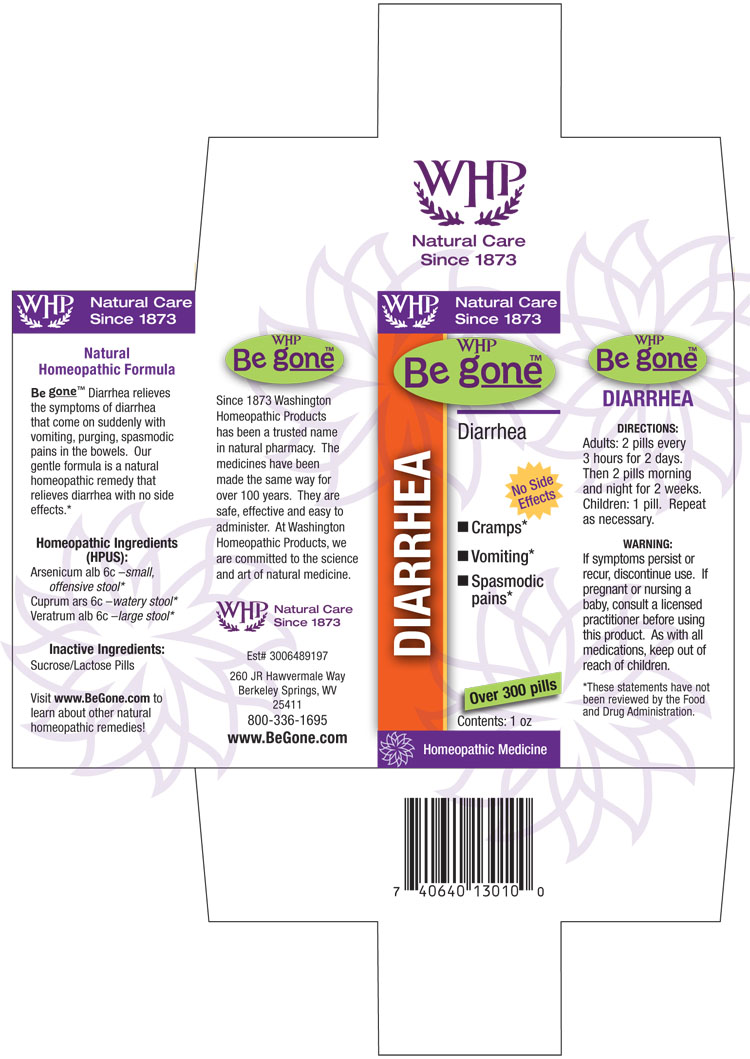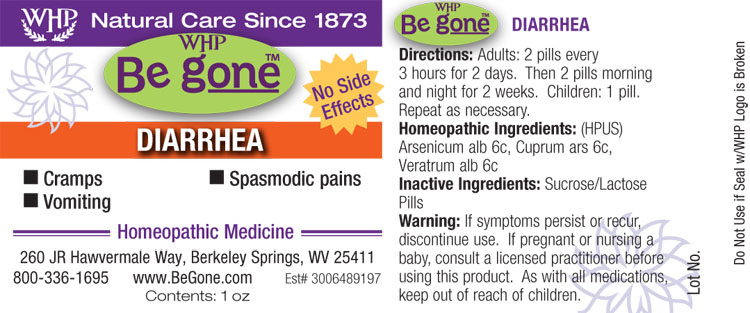 DRUG LABEL: WHP Be gone Diarrhea
NDC: 68428-745 | Form: PELLET
Manufacturer: Washington Homeopathic Products
Category: homeopathic | Type: HUMAN OTC DRUG LABEL
Date: 20140508

ACTIVE INGREDIENTS: ARSENIC TRIOXIDE 6 [hp_C]/1 1; CUPRIC ARSENITE 6 [hp_C]/1 1; VERATRUM ALBUM ROOT 6 [hp_C]/1 1
INACTIVE INGREDIENTS: SUCROSE; LACTOSE

DRUG FACTS

ACTIVE INGREDIENTS

ARSENICUM ALBUM

CUPRUM ARSENICUM

VERATRUM ALBUM

USES

Relieves the symptoms of diarrhea that come on suddenly with vomiting, purging, spasmodic pains in the bowels.

KEEP OUT OF REACH OF CHILDREN

As with all medications, keep out of reach of children.

INDICATIONS

Arsenicum alb 6c –small, offensive stool*

Cuprum ars 6c –watery stool*

Veratrum alb 6c –large stool*

■ Cramps* ■ Vomiting* ■ Spasmodic pains*

*These statements have not been reviewed by the Food and Drug Administration.

STOP USE AND ASK DOCTOR

If symptoms persist or recur, discontinue use. If pregnant or nursing a baby, consult a licensed practitioner before using this product.

DIRECTIONS

Adults: 2 pills every 3 hours for 2 days. Then 2 pills morning and night for 2 weeks. Children: 1 pill. Repeat as necessary.

INACTIVE INGREDIENTS

Sucrose/Lactose Pills